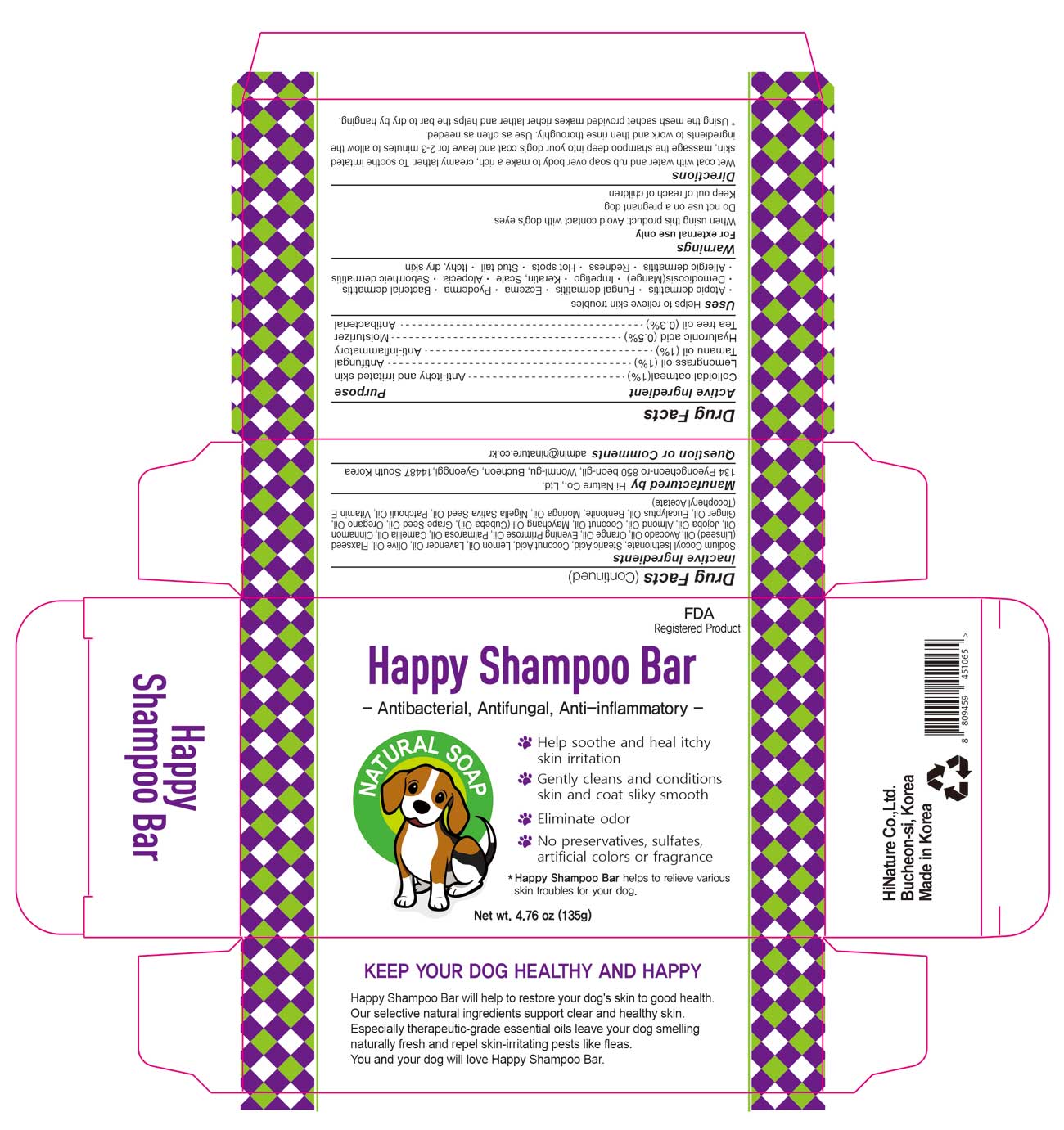 DRUG LABEL: Happy Bar
NDC: 86068-103 | Form: SOAP
Manufacturer: Hi Nature Co., Ltd.
Category: animal | Type: OTC ANIMAL DRUG LABEL
Date: 20180314

ACTIVE INGREDIENTS: OATMEAL 1.35 g/135 g; EAST INDIAN LEMONGRASS OIL 1.35 g/135 g; TAMANU OIL 1.35 g/135 g; HYALURONIC ACID 0.675 g/135 g; TEA TREE OIL 0.405 g/135 g
INACTIVE INGREDIENTS: SODIUM COCOYL ISETHIONATE; Stearic Acid; COCONUT ACID; Lemon Oil; Lavender Oil; Olive Oil; LINSEED OIL; Avocado Oil; ORANGE OIL; Evening Primrose Oil; PALMAROSA OIL; Camellia Oil; Cinnamon Oil; Jojoba Oil; Almond Oil; COCONUT OIL; Grape Seed Oil; OREGANO LEAF OIL; Ginger Oil; Eucalyptus Oil; .ALPHA.-TOCOPHEROL SUCCINATE, D-; Bentonite; NIGELLA SATIVA SEED OIL; PATCHOULI OIL

Happy Shampoo Bar

Active ingredients

Colloidal oatmeal (1%)

Lemongrass oil (1%)

Tamanu oil (1%)

Hyaluronic acid (0.5%)

Tea tree oil (0.3%)

Purpose

Anti-itchy and irritated skin

Anti-fungal

Anti-inflammatory

Moisturizer

Anti-baacterial

Uses

Helps to relieve skin troubles

♣ Allergic dermatitis ♣ Atopic dermatitis ♣ Bacterial dermatitis ♣ Eczema ♣ Fungal dermatitis ♣ Furrows of skin and foot-pad

♣ Keratin ♣ Scale ♣ Seborrheic dermatitis ♣ Alopecia ♣ Dandruff ♣ Redness ♣ Mange hot spot ♣ Ticks & Flea Dry skin

Directions

Wet coat with water and rub soap over body to make a rich, creamy lather. For comforting irritated skin, massage the shampoo deep into your dog’s coat and leave for 2-3 minutes to allow the ingredients to work and then rinse thoroughly. Use as often as needed.

* Using the mesh sachet provided makes more rich lather and helps dry in hanging.

Warnings

For external use only

When using this product ♣ Do not get into eyes.

Do not use during pregnancy

Keep out of reach of children

Inactive ingredients

Sodium Cocoyl Isethionate, Stearic Acid, Coconut Acid, Lemon Oil, Lavender Oil, Olive Oil, Flaxseed (Linseed) Oil, Avocado Oil, Orange Oil, Evening Primrose Oil, Palmrosa Oil, Camellia Oil, Cinnamon Oil, Jojoba Oil, Almond Oil, Coconut Oil, Maychang Oil (Cubeba Oil), Grape Seed Oil, Oregano Oil, Ginger Oil, Eucalyptus Oil, Vitamine E (Tocopheryl Acetate), Bentonite, Moringa Oil, Nigella Sativa Seed Oil, Patchouli Oil